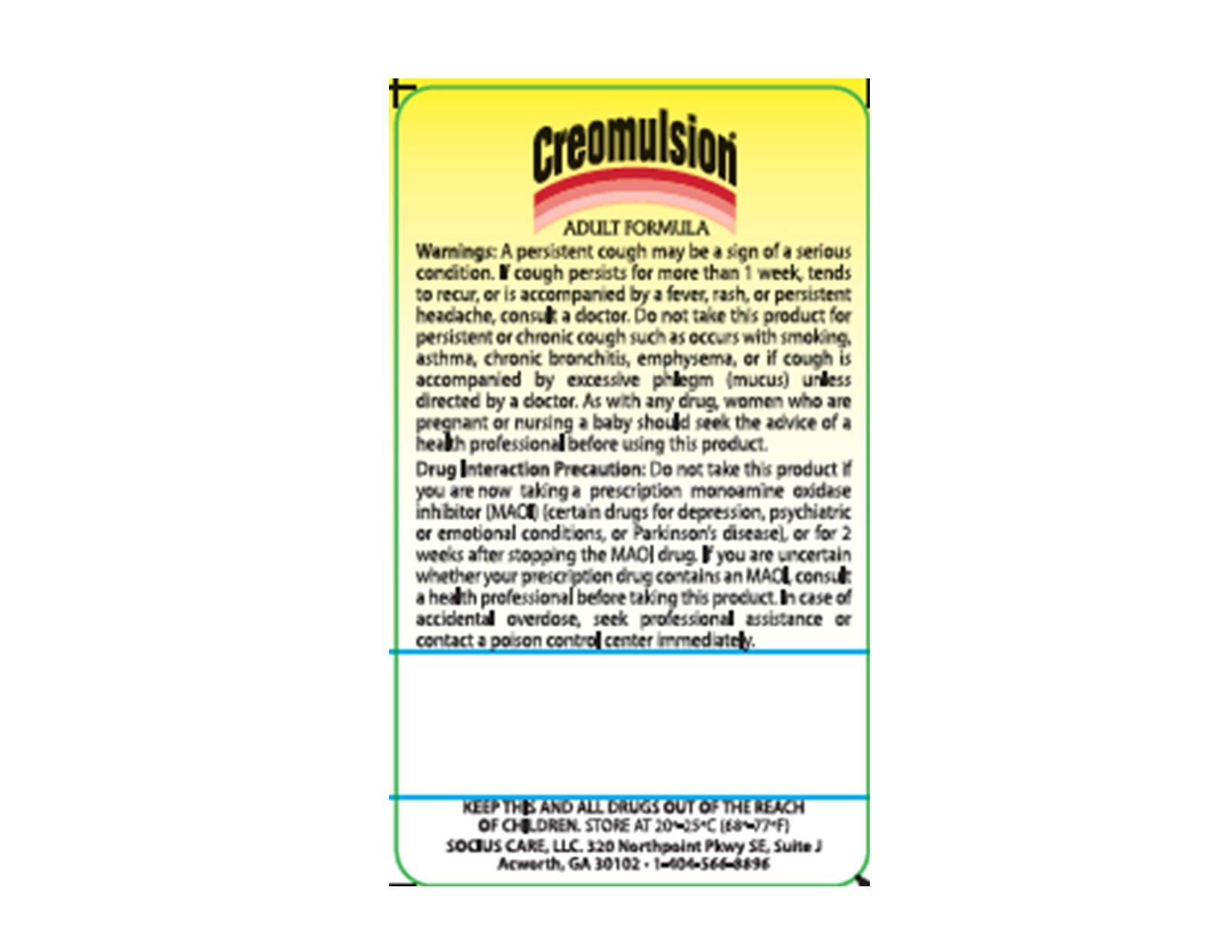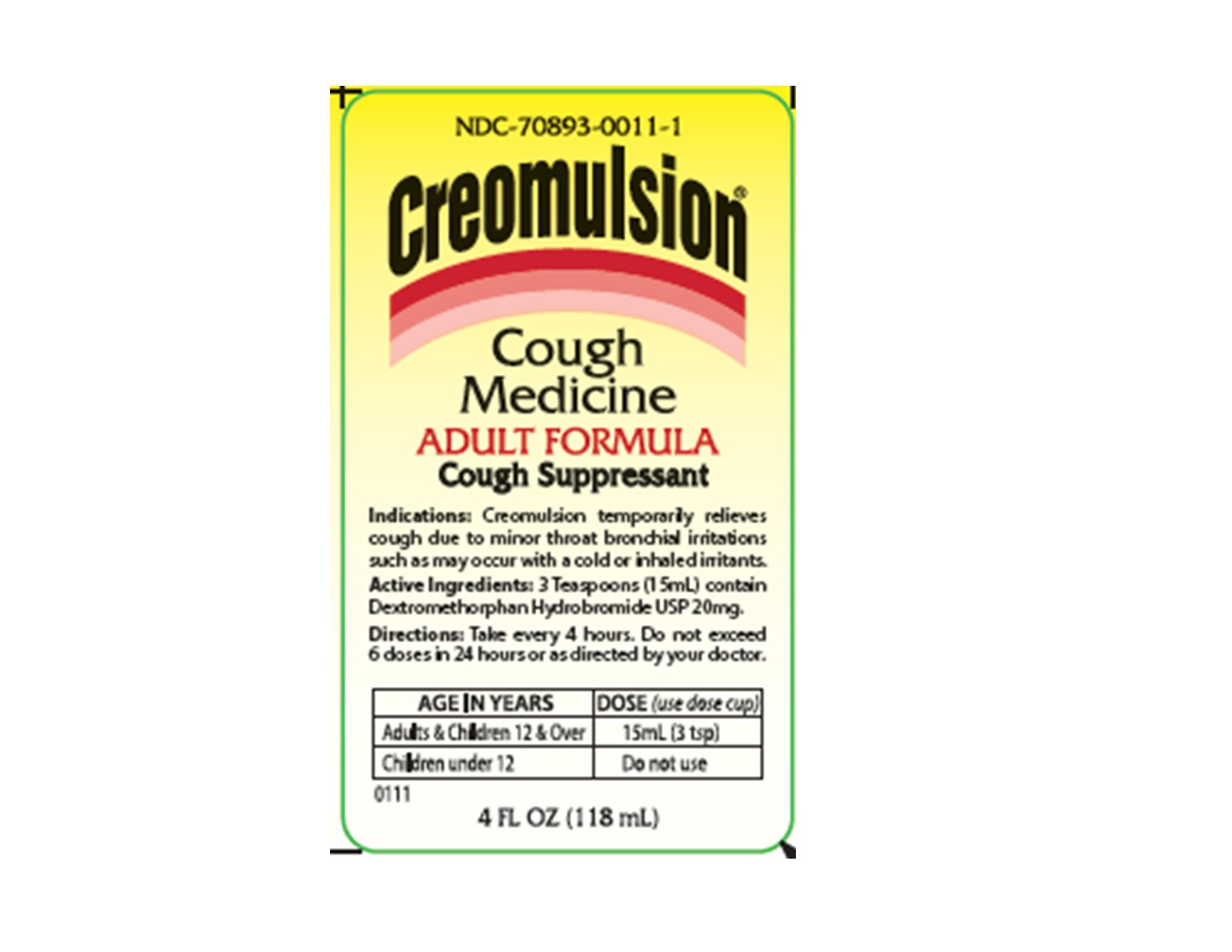 DRUG LABEL: Creomulsion
NDC: 70893-0011 | Form: SYRUP
Manufacturer: Socius Care, LLC
Category: otc | Type: HUMAN OTC DRUG LABEL
Date: 20260217

ACTIVE INGREDIENTS: DEXTROMETHORPHAN HYDROBROMIDE 20 mg/15 mL
INACTIVE INGREDIENTS: WOOD CREOSOTE; CARAMEL; CITRIC ACID MONOHYDRATE; CORN SYRUP; MENTHOL; POTASSIUM SORBATE; WATER; SODIUM BENZOATE; SUCROSE

Creomulsion Cough Medicine Adult Formula Drug Facts

Active Ingredient

In each (3 tsp) 15 ml Dextromethorphan HBr, USP 20 mg

Purpose

Cough Suppressant

Uses

- Temporarily relieves cough due to minor throat and bronchial irritation as may occur with a cold.

Warnings

Do not use if you are now taking prescription monoamine oxidase inhibitor (MAOI)

(certain drugs for depression, psychiatric; or emotional conditions, or Parkinson's disease),

or for 2 weeks after stopping the MAOI drug. If you do not know if your prescription drug contains an MAOI, ask a doctor or a pharmacist before taking this product.

Ask a doctor before use if you

- have cough that occurs with too much phlegm (mucus)
- have cough that lasts or is chronic such as occurs with smoking, asthma, chronic bronchitis, or emphysema.

Stop use and ask a doctor if

- cough lasts more than 7 days, comes back, or is accompanied by fever, rash, or persistent headache. These could be signs of a serious condition.

PREGNANCY OR BREAST FEEDING

If pregnant or breast feeding, ask a health professional before use.

Keep out of reach of children. In case of overdose, get medical help or contact a Poison Control Center right away.

Directions

•Do not take more than 6 doses in any 24 period. Use enclosed dose cup.

Adults and children 12 years and over | 15mL (3 tsp) every 4 hours
Children under 12 years | do not use

Other Information

- store at 20-25°C (68-77°F)

- packaged with tamper-evident seal under the cap

- contains no alcohol

- each 15 mL contains 5 mg sodium

Inactive ingredients

beechwood creosote, caramel, citric acid, corn syrup, menthol, potassium sorbate, purified water, sodium benzoate, sucrose

Questions or Comments

Call 8am - 4pm Est. Mon - Fri. 1-404-566-8896

Money Back Guarantee

Guaranteed to give desired results or your money back.

Send carton top, reason for dissatisfaction, sales receipt, lot number, and your phone number to Socius Care, LLC

3939 Royal Dr. NW, Suite 230, Kennesaw, GA 30144

DESCRIPTION

How Creomulsion Cough Medicine Works?

The Creomulsion Cough Medicine contains a safe and effective cough suppressant which acts by temporarily calming the cough control center to relieve coughs. Its rich, traditional base coats and soothes raw, irritated membranes. It contains no dyes, no alcohol, and no artificial sweeteners.